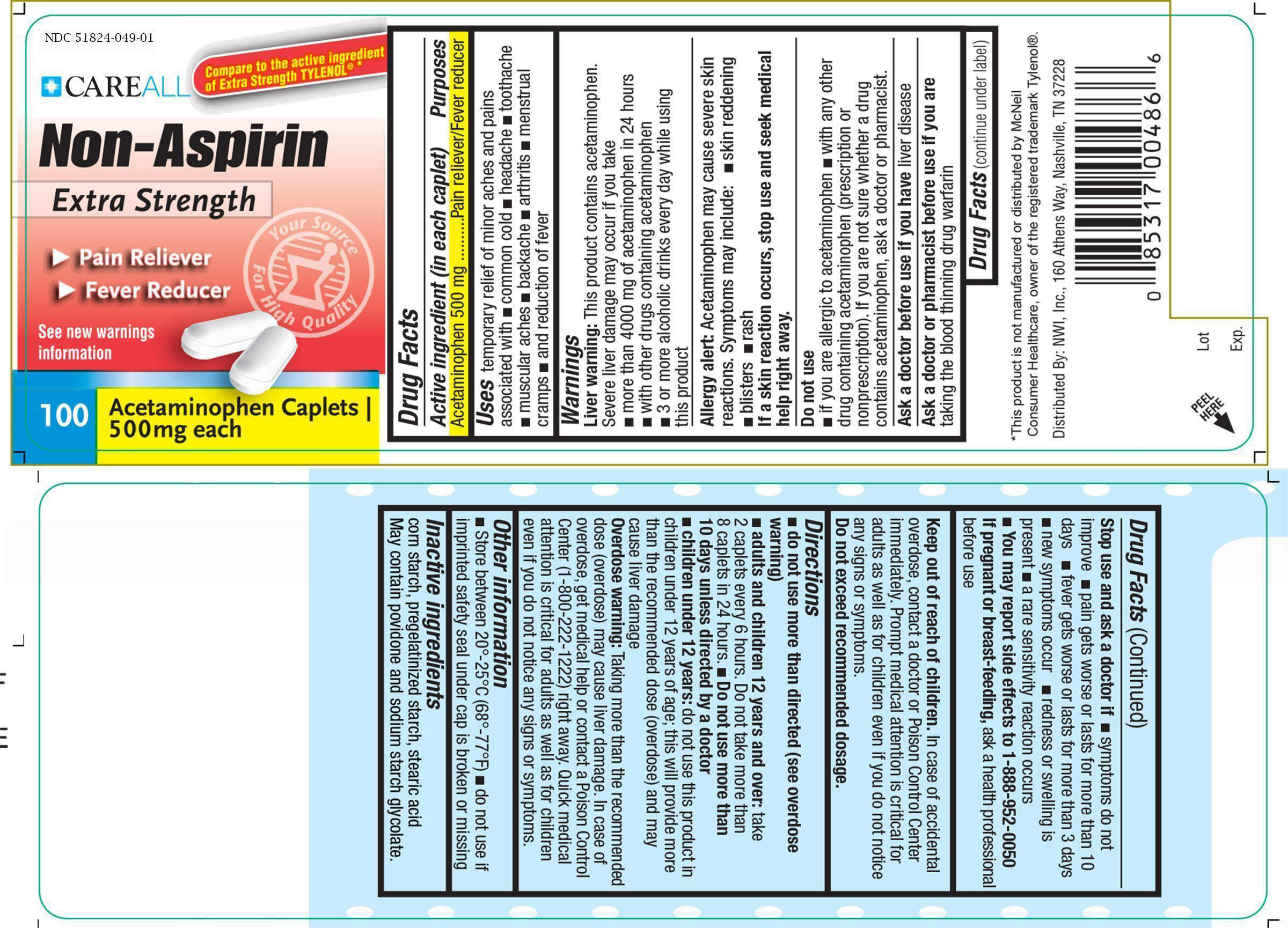 DRUG LABEL: CareALL Non Aspirin

NDC: 51824-049 | Form: TABLET
Manufacturer: New World Imports, Inc
Category: otc | Type: HUMAN OTC DRUG LABEL
Date: 20251201

ACTIVE INGREDIENTS: ACETAMINOPHEN 500 mg/1 1
INACTIVE INGREDIENTS: STARCH, CORN; PROPYLENE GLYCOL; STEARIC ACID; POVIDONE; SODIUM STARCH GLYCOLATE TYPE A CORN

Drug Facts

ACTIVE INGREDIENT

Acteminophen 500 mg

PURPOSE

Pain reliever / Fever reducer

KEEP OUT OF REACH OF CHILDREN

In case of accidental overdose, contact a doctor or Poison Control Center (1-800-222-1222) right away. Quick medical attention is critical for adults as well as for children even if you do not notice any signs or symptoms.

INDICATIONS AND USAGE

For the temporary relief of minor aches and pains associated with: the common cold, headache, toothache, muscular aches, backache, minor pain from arthritis, premenstural and menstrual cramps

Temporarily reduces fever

WARNINGS

Liver Warning:This product contains acetaminophen. Severe liver damage may occur if you take:

- more than 4000 mg of acetaminophen in 24 hours
- with other drugs containing acetaminophen
- 3 or more alcoholic drinks every day while using this product

Allergy Alert:Acetaminophen may cause severe skin reactions. Symptoms may include skin reddening, blisters, rash.

If a skin reaction occurs, stop use and seek medical help right away.

Do not use

- with any other drug containing acetaminophen (prescription or nonprescription). If you are not sure whether a drug contains acetaminophen, ask a doctor or pharmacist.
- if you are allergic to acetaminophen or any of the inactive ingredients in this product.

Ask a doctor before use if you haveliver disease

Ask a doctor or pharmacist before use if youare taking the blood thinning drug warfarin

Stop use and ask a doctor if:

- Pain gets worse or lasts for more than 10 days
- Fever gets worse or lasts for more than 3 days
- New symptoms occur
- Redness or swelling is present

These could be signs of a serious condition

If pregnant of breast-feeding,ask a health professional before use.

Do not exceed recommended dosage.

Do not use more than directed (see overdose warnings)

Adults and children 12 years of age and older:

- Take 2 caplets every 6 hours while symptoms last.
- Do not take more than 6 caplets in 24 hours, unless directed by a doctor.
- Do not use more than 10 days unless directed by a doctor.

Children under 12 years of age: consult a doctor

INACTIVE INGREDIENT

Corn Starch, povidone, pregelatinized starch, sodium starch glycolate, stearic acid